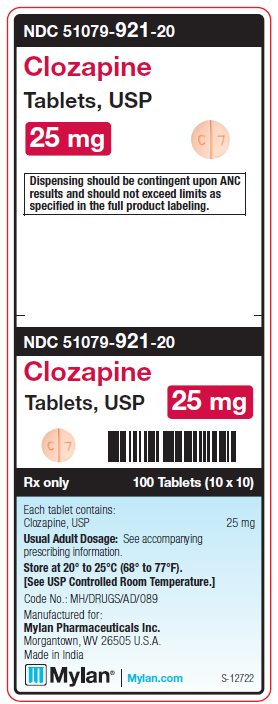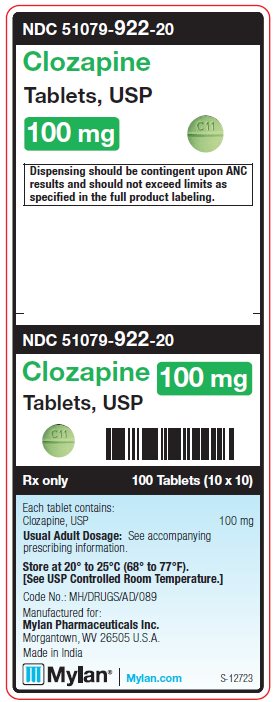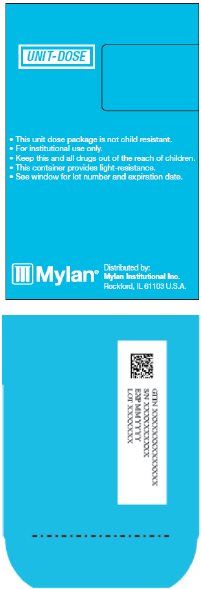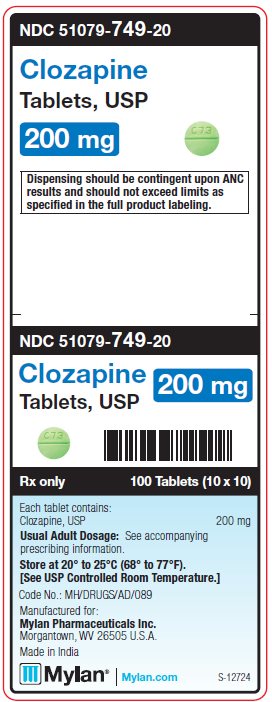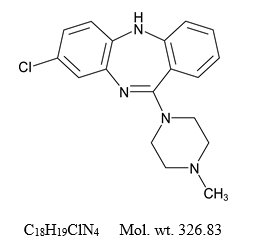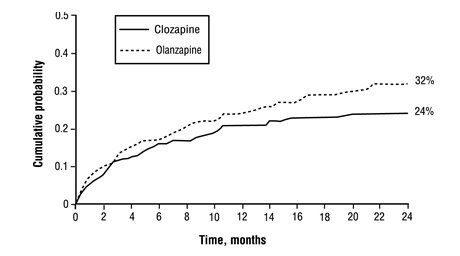 DRUG LABEL: Clozapine
NDC: 51079-921 | Form: TABLET
Manufacturer: Mylan Institutional Inc.
Category: prescription | Type: HUMAN PRESCRIPTION DRUG LABEL
Date: 20251111

ACTIVE INGREDIENTS: CLOZAPINE 25 mg/1 1
INACTIVE INGREDIENTS: SILICON DIOXIDE; CROSPOVIDONE, UNSPECIFIED; LACTOSE MONOHYDRATE; MAGNESIUM STEARATE; MICROCRYSTALLINE CELLULOSE; SODIUM LAURYL SULFATE; FD&C RED NO. 40

HIGHLIGHTS OF PRESCRIBING INFORMATION

These highlights do not include all the information needed to use CLOZAPINE TABLETS safely and effectively. See full prescribing information for CLOZAPINE TABLETS.
CLOZAPINE tablets, for oral use
Initial U.S. Approval: 1989

RECENT MAJOR CHANGES

Boxed Warning 1/2025
Warnings and Precautions (5.6) 1/2025

WARNING: SEVERE NEUTROPENIA; ORTHOSTATIC HYPOTENSION, BRADYCARDIA, AND SYNCOPE; SEIZURE; MYOCARDITIS, PERICARDITIS, AND CARDIOMYOPATHY; INCREASED MORTALITY IN ELDERLY PATIENTS WITH DEMENTIA-RELATED PSYCHOSIS

See full prescribing information for complete boxed warning.

- Severe Neutropenia: Clozapine tablets can cause severe neutropenia, which can lead to serious and fatal infections. Patients initiating and continuing treatment with clozapine tablets must have a baseline blood absolute neutrophil count (ANC) measured before treatment initiation and regular ANC monitoring during treatment (2.1, 5.1).
- Clozapine tablets are available only through a restricted program called the Clozapine REMS (5.2).
- Orthostatic Hypotension, Bradycardia, and Syncope: Risk is dose-related. Starting dose is 12.5 mg. Titrate gradually and use divided dosages. (2.2, 2.5, 5.3)
- Seizure: Risk is dose-related. Titrate gradually and use divided doses. Use with caution in patients with history of seizure or risk factors for seizure. (2.2, 5.5)
- Myocarditis, Pericarditis, Cardiomyopathy and Mitral Valve Incompetence: Can be fatal. Discontinue and obtain cardiac evaluation if findings suggest these cardiac reactions. (5.6)
- Increased Mortality in Elderly Patients with Dementia-Related Psychosis: Clozapine tablets are not approved for this condition. (5.7)

1 INDICATIONS AND USAGE

Clozapine tablets are an atypical antipsychotic indicated for:

- Treatment-resistant schizophrenia. Efficacy was established in an active-controlled study. (1.1, 14.1)
- Reducing suicidal behavior in patients with schizophrenia or schizoaffective disorder. Efficacy was established in an active-controlled study. (1.2, 14.2)

2 DOSAGE AND ADMINISTRATION

- Starting Dose: 12.5 mg once daily or twice daily. (2.2)
- Use cautious titration and divided dosage schedule. (2.2, 5.3)
- Titration: increase the total daily dosage in increments of 25 mg to 50 mg per day, if well-tolerated. (2.2)
- Target dose: 300 mg to 450 mg per day, in divided doses, by the end of 2 weeks. (2.2)
- Subsequent increases: increase in increments of 100 mg or less, once or twice weekly. (2.2)
- Maximum daily dose: 900 mg (2.2)

3 DOSAGE FORMS AND STRENGTHS

25 mg, 50 mg, 100 mg and 200 mg tablets with a functional score on one side (3)

4 CONTRAINDICATIONS

Known serious hypersensitivity to clozapine or any other component of clozapine tablets. (4)

5 WARNINGS AND PRECAUTIONS

- Gastrointestinal Hypomotility with Severe Complications:Severe gastrointestinal adverse reactions have occurred with the use of clozapine tablets. If constipation is identified, close monitoring and prompt treatment is advised. (5.8)
- Eosinophilia:Assess for organ involvement (e.g., myocarditis, pancreatitis, hepatitis, colitis, nephritis). Discontinue if these occur. (5.9)
- QT Interval Prolongation:Can be fatal. Consider additional risk factors for prolonged QT interval (disorders and drugs). (5.10)
- Metabolic Changes:Atypical antipsychotic drugs have been associated with metabolic changes that may increase cardiovascular/cerebrovascular risk.
  These metabolic changes include:
  - Hyperglycemia and Diabetes Mellitus:Monitor for symptoms of hyperglycemia including polydipsia, polyuria, polyphagia, and weakness. Monitor glucose regularly in patients with diabetes or at risk for diabetes. (5.11)
  - Dyslipidemia:Undesirable alterations in lipids have occurred in patients treated with atypical antipsychotics. (5.11)
  - Weight Gain:Significant weight gain has occurred. Monitor weight gain. (5.11)
- Neuroleptic Malignant Syndrome (NMS):Immediately discontinue and monitor closely. Assess for co-morbid conditions. (5.12)
- Hepatotoxicity:Can be fatal. Monitor for hepatotoxicity. Discontinue treatment if hepatitis or transaminase elevations combined with other symptoms occur (5.13).
- Fever:Evaluate for infection and for neutropenia, NMS. (5.14)
- Pulmonary Embolism (PE):Consider PE if respiratory distress, chest pain, or deep-vein thrombosis occur. (5.15)
- Anticholinergic Toxicity:When possible, avoid use with other anticholinergic drugs and use with caution in patients with a current diagnosis or prior history of constipation, urinary retention, clinically significant prostatic hypertrophy, or other conditions in which anticholinergic effects can lead to significant adverse reactions. (5.16, 7.1)
- Interference with Cognitive and Motor Performance:Advise caution when operating machinery, including automobiles. (5.17)

6 ADVERSE REACTIONS

Most common adverse reactions (≥ 5%) were: CNS reactions (sedation, dizziness/vertigo, headache, and tremor); cardiovascular reactions (tachycardia, hypotension, and syncope); autonomic nervous system reactions (hypersalivation, sweating, dry mouth, and visual disturbances); gastrointestinal reactions (constipation and nausea); and fever. (6.1)

To report SUSPECTED ADVERSE REACTIONS, contact Mylan at 1-877-446-3679 (1-877-4-INFO-RX) or FDA at 1-800-FDA-1088 or www.fda.gov/medwatch.

7 DRUG INTERACTIONS

- Concomitant use of Strong CYP1A2 Inhibitors:Reduce clozapine tablets dose to one-third when coadministered with strong CYP1A2 inhibitors (e.g., fluvoxamine, ciprofloxacin, enoxacin). (2.6, 7.1)
- Concomitant use of Strong CYP3A4 Inducersis not recommended. (2.6, 7.1)
- Discontinuation of CYP1A2 or CYP3A4 Inducers:Consider reducing clozapine tablets dose when CYP1A2 inducers (e.g., tobacco smoke) or CYP3A4 inducers (e.g., carbamazepine) are discontinued. (2.6, 7.1)
- Anticholinergic drugs: Concomitant use may increase the risk for anticholinergic toxicity. (5.8, 5.16, 7.1)

8 USE IN SPECIFIC POPULATIONS

- Pregnancy: May cause extrapyramidal and/or withdrawal symptoms in neonates with third trimester exposure. (8.1)

FULL PRESCRIBING INFORMATION

WARNING: SEVERE NEUTROPENIA; ORTHOSTATIC HYPOTENSION, BRADYCARDIA, AND SYNCOPE; SEIZURE; MYOCARDITIS, PERICARDITIS, AND CARDIOMYOPATHY; INCREASED MORTALITY IN ELDERLY PATIENTS WITH DEMENTIA-RELATED PSYCHOSIS

Severe Neutropenia

Clozapine tablets treatment has caused severe neutropenia, defined as an absolute neutrophil count (ANC) less than 500/μL. Severe neutropenia can lead to serious infection and death. Prior to initiating treatment with clozapine tablets a baseline ANC must be at least 1500/μL for the general population; and must be at least 1000/μL for patients with documented Benign Ethnic Neutropenia (BEN). During treatment, patients must have regular ANC monitoring. Advise patients to immediately report symptoms consistent with severe neutropenia or infection (e.g., fever, weakness, lethargy, or sore throat) [see Dosage and Administration (2.1)and Warnings and Precautions (5.1)].

Because of the risk of severe neutropenia, clozapine tablets are available only through a restricted program under a Risk Evaluation Mitigation Strategy (REMS) called the Clozapine REMS Program [see Warnings and Precautions (5.2)] .

Orthostatic Hypotension, Bradycardia, Syncope

Orthostatic hypotension, bradycardia, syncope, and cardiac arrest have occurred with clozapine tablets treatment. The risk is highest during the initial titration period, particularly with rapid dose escalation. These reactions can occur with the first dose, with doses as low as 12.5 mg per day, or when restarting patients who have had even a brief interruption in treatment with clozapine tablets. Initiate treatment at 12.5 mg once or twice daily; titrate slowly; and use divided dosages to minimize risk. Use clozapine tablets cautiously in patients with cardiovascular or cerebrovascular disease or conditions predisposing to hypotension (e.g., dehydration, use of antihypertensive medications) [see Dosage and Administration (2.2, 2.5), Warnings and Precautions (5.3)] .

Seizures

Seizures have occurred with clozapine tablets treatment. The risk is dose- related. Initiate treatment at 12.5 mg, titrate gradually, and use divided dosing. Use caution when administering clozapine tablets to patients with a history of seizures or other predisposing risk factors for seizure (CNS pathology, medications that lower the seizure threshold, alcohol abuse). Caution patients about engaging in any activity where sudden loss of consciousness could cause serious risk to themselves or others [see Dosage and Administration (2.2), Warnings and Precautions (5.5)] .

Myocarditis, Pericarditis, Cardiomyopathy and Mitral Valve Incompetence

Fatalmyocarditis and cardiomyopathy have occurred with clozapine tablets treatment. Discontinue clozapine tablets and obtain a cardiac evaluation upon suspicion of these reactions. Generally, patients with clozapine tablets-related myocarditis or cardiomyopathy should not be rechallenged with clozapine tablets. Consider the possibility of myocarditis, pericarditis, or cardiomyopathy if chest pain, tachycardia, palpitations, dyspnea, fever, flu-like symptoms, hypotension, or ECG changes occur [see Warnings and Precautions (5.6)] .

Increased Mortality in Elderly Patients with Dementia-Related Psychosis

Elderly patients with dementia-related psychosis treated with antipsychotic drugs are at an increased risk of death. Clozapine tablets are not approved for use in patients with dementia-related psychosis [see Warnings and Precautions (5.7)] .

1 INDICATIONS AND USAGE

1.1 Treatment-Resistant Schizophrenia

Clozapine tablets are indicated for the treatment of severely ill patients with schizophrenia who fail to respond adequately to standard antipsychotic treatment. Because of the risks of severe neutropenia and of seizure associated with its use, clozapine tablets should be used only in patients who have failed to respond adequately to standard antipsychotic treatment [see Warnings and Precautions (5.1, 5.5)] .

The effectiveness of clozapine tablets in treatment-resistant schizophrenia was demonstrated in a 6-week, randomized, double-blind, active-controlled study comparing clozapine tablets and chlorpromazine in patients who had failed other antipsychotics [see Clinical Studies (14.1)] .

1.2 Reduction in the Risk of Recurrent Suicidal Behavior in Schizophrenia or Schizoaffective Disorder

Clozapine tablets are indicated for reducing the risk of recurrent suicidal behavior in patients with schizophrenia or schizoaffective disorder who are judged to be at chronic risk for re-experiencing suicidal behavior, based on history and recent clinical state. Suicidal behavior refers to actions by a patient that put him/herself at risk for death.

The effectiveness of clozapine tablets in reducing the risk of recurrent suicidal behavior was demonstrated over a two-year treatment period in the InterSePT™ trial [see Clinical Studies (14.2)] .

2 DOSAGE AND ADMINISTRATION

2.1 Required Laboratory Testing Prior to Initiation and During Therapy

Prior to initiating treatment with clozapine tablets, a baseline ANC must be obtained. The baseline ANC must be at least 1500/μL for the general population, and at least 1000/μL for patients with documented Benign Ethnic Neutropenia (BEN). To continue treatment, the ANC must be monitored regularly [see Warnings and Precautions (5.1)] .

2.2 Dosing Information

The starting dose is 12.5 mg once daily or twice daily. The total daily dose can be increased in increments of 25 mg to 50 mg per day, if well-tolerated, to achieve a target dose of 300 mg to 450 mg per day (administered in divided doses) by the end of 2 weeks. Subsequently, the dose can be increased once weekly or twice weekly, in increments of up to 100 mg. The maximum dose is 900 mg per day. To minimize the risk of orthostatic hypotension, bradycardia, and syncope, it is necessary to use this low starting dose, gradual titration schedule, and divided dosages [see Warnings and Precautions (5.3)] .

Clozapine tablets can be taken with or without food [see Pharmacokinetics (12.3)] .

2.3 Maintenance Treatment

Generally, patients responding to clozapine tablets should continue maintenance treatment on their effective dose beyond the acute episode.

2.4 Discontinuation of Treatment

Method of treatment discontinuation will vary depending on the patient’s last ANC:

- See Tables 2 or 3 for appropriate ANC monitoring based on the level of neutropenia if abrupt treatment discontinuation is necessary because of moderate to severe neutropenia.
- Reduce the dose gradually over a period of 1 to 2 weeks if termination of clozapine tablets therapy is planned and there is no evidence of moderate to severe neutropenia.
- For abrupt clozapine discontinuation for a reason unrelated to neutropenia, continuation of the existing ANC monitoring is recommended for general population patients until their ANC is ≥ 1500/μL and for BEN patients until their ANC is ≥ 1000/μL or above their baseline.
- Additional ANC monitoring is required for any patient reporting onset of fever (temperature of 38.5°C or 101.3°F, or greater) during the 2 weeks after discontinuation [see Warnings and Precautions (5.1)].
- Monitor all patients carefully for the recurrence of psychotic symptoms and symptoms related to cholinergic rebound such as profuse sweating, headache, nausea, vomiting, and diarrhea.

2.5 Re-Initiation of Treatment

When restarting clozapine tablets in patients who have had even a brief interruption in treatment with clozapine tablets dosage must be reduced. This is necessary to minimize the risk of hypotension, bradycardia, and syncope [see Warnings and Precautions (5.3)] . If one day’s dosing has been missed, resume treatment at 40% to 50% of the established dose. If two days dosing have been missed, resume dose at approximately 25% of the established dosage. For longer interruptions, re-initiate at a dosage of 12.5 mg once daily or twice daily. If these dosages are well-tolerated, the dosage may be increased to the previous dosage more quickly than recommended for initial treatment.

2.6 Dosage Adjustments with Concomitant Use of CYP1A2, CYP2D6, CYP3A4 Inhibitors or CYP1A2, CYP3A4 Inducers

Dose adjustments may be necessary in patients with concomitant use of: strong CYP1A2 inhibitors (e.g., fluvoxamine, ciprofloxacin, or enoxacin); moderate or weak CYP1A2 inhibitors (e.g., oral contraceptives, or caffeine); CYP2D6 or CYP3A4 inhibitors (e.g., cimetidine, escitalopram, erythromycin, paroxetine, bupropion, fluoxetine, quinidine, duloxetine, terbinafine, or sertraline); CYP3A4 inducers (e.g., phenytoin, carbamazepine, St. John’s wort, and rifampin); or CYP1A2 inducers (e.g., tobacco smoking) (Table 1) [see Drug Interactions (7)] .

Table 1. Dose Adjustment in Patients Taking Concomitant Medications
Co-medications | Scenarios
 | Initiating clozapine tablets while taking a co-medication | Adding a co-medication while taking clozapine tablets | Discontinuing a co-medication while continuing clozapine tablets
Strong CYP1A2 Inhibitors | Use one-third of the clozapine tablets dose. |  | Increase clozapine tablets dose based on clinical response.
Moderate or Weak; CYP1A2 Inhibitors | Monitor for adverse reactions. Consider reducing the clozapine tablets dose if necessary. |  | Monitor for lack of effectiveness. Consider increasing clozapine tablets dose if necessary.
CYP2D6 or CYP3A4 Inhibitors
Strong CYP3A4 Inducers | Concomitant use is not recommended. However, if the inducer is necessary, it may be necessary to increase the clozapine tablets dose. Monitor for decreased effectiveness. |  | Reduce clozapine tablets dose based on clinical response.
Moderate or weak CYP1A2 or CYP3A4 Inducers | Monitor for decreased effectiveness. Consider increasing the clozapine tablets dose if necessary. |  | Monitor for adverse reactions. Consider reducing the clozapine tablets dose if necessary.

2.7 Renal or Hepatic Impairment or CYP2D6 Poor Metabolizers

It may be necessary to reduce the clozapine tablets dose in patients with significant renal or hepatic impairment, or in CYP2D6 poor metabolizers [see Use in Specific Populations (8.6, 8.7)] .

3 DOSAGE FORMS AND STRENGTHS

Clozapine Tablets, USP are available containing 25 mg, 50 mg, 100 mg or 200 mg of clozapine, USP.

- The 25 mg tablets are peach, round, functionally scored tablets debossed with Cto the left of the score and 7to the right of the score on one side of the tablet and Mon the other side.
- The 50 mg tablets are green, round, functionally scored tablets debossed with C72above the score and blank below the score on one side of the tablet and Mon the other side.
- The 100 mg tablets are green, round, functionally scored tablets debossed with C11above the score and blank below the score on one side of the tablet and Mon the other side.
- The 200 mg tablets are green, round, functionally scored tablets debossed with C73above the score and blank below the score on one side of the tablet and Mon the other side.

4 CONTRAINDICATIONS

Clozapine tablets are contraindicated in patients with a history of serious hypersensitivity to clozapine (e.g., photosensitivity, vasculitis, erythema multiforme, or Stevens-Johnson Syndrome) or any other component of clozapine tablets [see Adverse Reactions (6.2)] .

5 WARNINGS AND PRECAUTIONS

5.1 Severe Neutropenia

Background

Clozapine tablets can cause neutropenia (a low absolute neutrophil count (ANC)), defined as a reduction below pre-treatment normal levels of blood neutrophils. The ANC is usually available as a component of the complete blood count (CBC), including differential, and is more relevant to drug-induced neutropenia than is the white blood cell (WBC) count. The ANC may also be calculated using the following formula: ANC equals the Total WBC count multiplied by the total percentage of neutrophils obtained from the differential (neutrophil “segs” plus neutrophil “bands”).Other granulocytes (basophils and eosinophils) contribute minimally to neutropenia and their measurement is not necessary [see Adverse Reactions (6.2)] . Neutropenia may be mild, moderate, or severe (see Tables 2 and 3). To improve and standardize understanding, “severe neutropenia” replaces the previous terms severe leukopenia, severe granulocytopenia, or agranulocytosis.

Severe neutropenia, ANC less than (<) 500/μL, occurs in a small percentage of patients taking clozapine tablets and is associated with an increase in the risk of serious and potentially fatal infections. Risk of neutropenia appears greatest during the first 18 weeks on treatment and then declines. The mechanism by which clozapine tablets cause neutropenia is unknown and is not dose-dependent.

Two separate management algorithms are provided below, the first for patients in the general population, and the second for patients identified to have baseline neutropenia.

Clozapine Tablets Treatment and Monitoring in the General Patient Population (see Table 2)

Obtain a CBC, including the ANC value, prior to initiating treatment with clozapine tablets to ensure the presence of a normal baseline neutrophil count (equal to or greater than 1500/μL) and to permit later comparisons. Patients in the general population with an ANC equal to or greater than (≥) 1500/μL are considered within normal range (Table 2) and are eligible to initiate treatment. Weekly ANC monitoring is required for all patients during the first 6 months of treatment. If a patient’s ANC remains equal to or greater than 1500/μL for the first 6 months of treatment, monitoring frequency may be reduced to every 2 weeks for the next 6 months. If the ANC remains equal to or greater than 1500/μL for the second 6 months of continuous therapy, ANC monitoring frequency may be reduced to once every 4 weeks thereafter.

Table 2. Clozapine Tablets Treatment Recommendations Based on Absolute Neutrophil Count (ANC) Monitoring for the General Patient Population
ANC Level | Clozapine Tablets Treatment Recommendations | ANC Monitoring
Normal range (≥ 1500/μL) | - Initiate treatment - If treatment interrupted: - < 30 days, continue monitoring as before - ≥ 30 days, monitor as if new patient | - Weekly from initiation to 6 months - Every 2 weeks from 6 to 12 months - Monthly after 12 months
Normal range (≥ 1500/μL) | - Discontinuation for reasons other than neutropenia | - See Section 2.4
Mild Neutropenia (1000 to 1499/μL) [Confirm all initial reports of ANC less than 1500/µL with a repeat ANC measurement within 24 hours] | - Continue treatment | - Three times weekly until ANC ≥ 1500/μL - Once ANC ≥ 1500/μL, return to patient’s last “Normal Range” ANC monitoring interval [If clinically appropriate]
Moderate Neutropenia (500 to 999/µL) | - Recommend hematology consultation - Interrupt treatment for suspected clozapine induced neutropenia - Resume treatment once ANC ≥ 1000/µL | - Daily until ANC ≥ 1000/µL, then - Three times weekly until ANC ≥ 1500/µL - Once ANC ≥ 1500/µL, check ANC weekly for 4 weeks, then return to patient’s last “Normal Range” ANC monitoring interval
Severe Neutropenia (less than 500/µL) | - Recommend hematology consultation - Interrupt treatment for suspected clozapine-induced neutropenia - Do not rechallenge unless prescriber determines benefits outweigh risks | - Daily until ANC ≥ 1000/µL, then - Three times weekly until ANC ≥ 1500/µL - If patient rechallenged, resume treatment as a new patient under “Normal Range” monitoring once ANC ≥ 1500/µL

Clozapine Tablets Treatment and Monitoring in Patients with Benign Ethnic Neutropenia (see Table 3)

Benign ethnic neutropenia (BEN) is a condition observed in certain ethnic groups whose average ANC values are lower than “standard” laboratory ranges for neutrophils. It is most commonly observed in individuals of African descent (approximate prevalence of 25-50%), some Middle Eastern ethnic groups, and in other non-Caucasian ethnic groups with darker skin. BEN is more common in men. Patients with BEN have normal hematopoietic stem-cell number and myeloid maturation, are healthy, and do not suffer from repeated or severe infections. They are not at increased risk for developing clozapine tablets-induced neutropenia. Additional evaluation may be needed to determine if baseline neutropenia is due to BEN. Consider hematology consultation before initiating or during clozapine tablets treatment as necessary.

Patients with BEN require a different ANC algorithm for clozapine tablets management due to their lower baseline ANC levels. Table 3 provides guidelines for managing clozapine tablets treatment and ANC monitoring in patients with BEN.

Table 3. Patients with Benign Ethnic Neutropenia (BEN); Clozapine Tablets Treatment Recommendations Based on Absolute Neutrophil Count (ANC) Monitoring
ANC Level | Treatment Recommendations | ANC Monitoring
Normal BEN Range (Established ANC baseline ≥ 1000/µL) | - Obtain at least two baseline ANC levels before initiating treatment - If treatment interrupted - < 30 days, continue monitoring as before - ≥ 30 days, monitor as if new patient | - Weekly from initiation to 6 months - Every 2 weeks from 6 to 12 months - Monthly after 12 months
Normal BEN Range (Established ANC baseline ≥ 1000/µL) | - Discontinuation of treatment for reasons other than neutropenia | - See Section 2.4
BEN Neutropenia 500 to 999/µL [Confirm all initial reports of ANC less than 1500/µL with a repeat ANC measurement within 24 hours] | - Recommend hematology consultation - Continue treatment | - Three times weekly until ANC ≥1000/µL or ≥ patient’s known baseline - Once ANC ≥ 1000/µL or at patient’s known baseline, check ANC weekly for 4 weeks, then return to patient’s last “Normal BEN Range” ANC monitoring interval. [If clinically appropriate]
BEN Severe Neutropenia less than 500/µL | - Recommend hematology consultation - Interrupt treatment for suspected clozapine-induced neutropenia - Do not rechallenge unless prescriber determines benefits outweigh risks | - Daily until ANC ≥ 500/µL, then - Three times weekly until ANC ≥ patient’s baseline - If patient rechallenged, resume treatment as a new patient under “Normal Range” monitoring once ANC ≥ 1000/µL or at patient’s baseline

General Guidelines for Management of All Patients with Fever or with Neutropenia

- Fever: Interrupt clozapine tablets as a precautionary measure in any patient who develops fever, defined as a temperature of 38.5°C [101.3°F] or greater, and obtain an ANC level. Fever is often the first sign of neutropenic infection.
- ANC less than 1000/µL: If fever occurs in any patient with an ANC less than 1000/µL, initiate appropriate workup and treatment for infection and refer to Tables 2 or 3 for management.
- Consider hematology consultation.
- See Neuroleptic Malignant Syndrome [NMS] and Fever under WARNINGS and PRECAUTIONS (5)and Instructions for Patients, under PATIENT COUNSELING INFORMATION (17).

Rechallenge After an ANC Less Than 500/µL (Severe Neutropenia)

For some patients who experience severe clozapine tablets-related neutropenia, the risk of serious psychiatric illness from discontinuing clozapine tablets treatment may be greater than the risk of rechallenge (e.g., patients with severe schizophrenic illness who have no treatment options other than clozapine tablets). A hematology consultation may be useful in deciding to rechallenge a patient. In general, however, do not rechallenge patients who develop severe neutropenia with clozapine tablets or a clozapine product.

If a patient will be rechallenged, the clinician should consider thresholds provided in Tables 2 and 3, the patient’s medical and psychiatric history, a discussion with the patient and his/her caregiver about the benefits and risks of clozapine tablets rechallenge, and the severity and characteristics of the neutropenic episode.

Using Clozapine Tablets with Other Drugs Associated with Neutropenia

It is unclear if concurrent use of other drugs known to cause neutropenia increases the risk or severity of clozapine tablets-induced neutropenia. There is no strong scientific rationale to avoid clozapine tablets treatment in patients concurrently treated with these drugs. If clozapine tablets are used concurrently with an agent known to cause neutropenia (e.g., some chemotherapeutic agents), consider monitoring patients more closely than the treatment guidelines provided in Tables 2 and 3. Consult with the treating oncologist in patients receiving concomitant chemotherapy.

5.2 Clozapine REMS Program

Clozapine tablets are only available through a restricted program under a REMS called the Clozapine REMS Program because of the risk of severe neutropenia.

Notable requirements of the Clozapine REMS Program include:

- Healthcare professionals who prescribe clozapine tablets must be certified with the program by enrolling and completing training
- Patients who receive clozapine tablets must be enrolled in the program and comply with the ANC testing and monitoring requirements
- Pharmacies dispensing clozapine tablets must be certified with the program by enrolling and completing training and must only dispense to patients who are eligible to receive clozapine tablets

Further information is available at www.clozapineREMS.com or 1-888-586-0758.

5.3 Orthostatic Hypotension, Bradycardia, and Syncope

Hypotension, bradycardia, syncope, and cardiac arrest have occurred with clozapine treatment. The risk is highest during the initial titration period, particularly with rapid dose-escalation. These reactions can occur with the first dose, at doses as low as 12.5 mg. These reactions can be fatal. The syndrome is consistent with neurally mediated reflex bradycardia (NMRB).

Treatment must begin at a maximum dose of 12.5 mg once daily or twice daily. The total daily dose can be increased in increments of 25 mg to 50 mg per day, if well-tolerated, to a target dose of 300 mg to 450 mg per day (administered in divided doses) by the end of 2 weeks. Subsequently, the dose can be increased weekly or twice weekly, in increments of up to 100 mg. The maximum dose is 900 mg per day. Use cautious titration and a divided dosage schedule to minimize the risk of serious cardiovascular reactions [see Dosage and Administration (2.2)] . Consider reducing the dose if hypotension occurs. When restarting clozapine tablets in patients who have had even a brief interruption in treatment with clozapine tablets, the dosage must be reduced. This is necessary to minimize the risk of hypotension, bradycardia, and syncope [see Dosage and Administration (2.5)] .

Use clozapine tablets cautiously in patients with cardiovascular disease (history of myocardial infarction or ischemia, heart failure, or conduction abnormalities), cerebrovascular disease, and conditions which would predispose patients to hypotension (e.g., concomitant use of antihypertensives, dehydration and hypovolemia).

5.4 Falls

Clozapine tablets may cause somnolence, postural hypotension, motor and sensory instability, which may lead to falls and, consequently, fractures or other injuries. For patients with diseases, conditions, or medications that could exacerbate these effects, complete fall risk assessments when initiating antipsychotic treatment and recurrently for patients on long-term antipsychotic therapy.

5.5 Seizures

Seizure has been estimated to occur in association with clozapine use at a cumulative incidence at one year of approximately 5%, based on the occurrence of one or more seizures in 61 of 1743 patients exposed to clozapine during its clinical testing prior to domestic marketing (i.e., a crude rate of 3.5%). The risk of seizure is dose-related. Initiate treatment with a low dose (12.5 mg), titrate slowly, and use divided dosing.

Use caution when administering clozapine tablets to patients with a history of seizures or other predisposing risk factors for seizure (e.g., head trauma or other CNS pathology, use of medications that lower the seizure threshold, or alcohol abuse). Because of the substantial risk of seizure associated with clozapine tablets use, caution patients about engaging in any activity where sudden loss of consciousness could cause serious risk to themselves or others (e.g., driving an automobile, operating complex machinery, swimming, climbing).

5.6 Myocarditis, Pericarditis, Cardiomyopathy and Mitral Valve Incompetence

Myocarditis, pericarditis, and cardiomyopathy have occurred with the use of clozapine tablets. These reactions can be fatal. Discontinue clozapine tablets and obtain a cardiac evaluation upon suspicion of myocarditis or cardiomyopathy. Generally, patients with a history of clozapine-associated myocarditis or cardiomyopathy should not be rechallenged with clozapine tablets. However, if the benefit of clozapine tablets treatment is judged to outweigh the potential risks of recurrence, the clinician may consider rechallenge with clozapine tablets in consultation with a cardiologist.

Myocarditis and pericarditis most frequently present within the first 2 months of clozapine treatment. Symptoms of cardiomyopathy generally occur later than clozapine-associated myocarditis and usually after 8 weeks of treatment. However, myocarditis, pericarditis, and cardiomyopathy can occur at any period during treatment with clozapine tablets. In patients who are diagnosed with cardiomyopathy while taking clozapine tablets, mitral valve incompetence has been reported.

5.7 Increased Mortality in Elderly Patients with Dementia-Related Psychosis

Elderly patients with dementia-related psychosis treated with antipsychotic drugs are at an increased risk of death. Analyses of 17 placebo-controlled trials (modal duration of 10 weeks), largely in patients taking atypical antipsychotic drugs, revealed a risk of death in drug-treated patients of between 1.6 to 1.7 times the risk of death in placebo-treated patients. Over the course of a typical 10-week controlled trial, the rate of death in drug-treated patients was about 4.5%, compared to a rate of about 2.6% in the placebo group. Although the causes of death were varied, most of the deaths appeared to be either cardiovascular (e.g., heart failure, sudden death) or infectious (e.g., pneumonia) in nature. Observational studies suggest that, similar to atypical antipsychotic drugs, treatment with conventional antipsychotic drugs may increase mortality in this population. The extent to which the findings of increased mortality in observational studies may be attributed to the antipsychotic drug as opposed to some characteristic(s) of the patients is not clear. Clozapine tablets are not approved for the treatment of patients with dementia-related psychosis [see Boxed Warning] .

5.8 Gastrointestinal Hypomotility with Severe Complications

Severe gastrointestinal adverse reactions have occurred with the use of clozapine tablets, primarily due to their potent anticholinergic effects and resulting gastrointestinal hypomotility. In post marketing experience, reported effects range from constipation to paralytic ileus. Increased frequency of constipation and delayed diagnosis and treatment increased the risk of severe complications of gastrointestinal hypomotility, which can result in fecal impaction, megacolon and intestinal obstruction, ischemia, infarction, perforation, ulceration, or necrosis [see Adverse Reaction (6.2)] . These reactions have resulted in hospitalization, surgery, and death. The risk of severe adverse reactions is further increased with anticholinergic medications (and other medications that decrease gastrointestinal peristalsis); therefore, concomitant use should be avoided when possible [see Warnings and Precautions (5.16), Drug Interactions (7.1)] .

Prior to initiating clozapine tablets, screen for constipation and treat as necessary. Subjective symptoms of constipation may not accurately reflect the degree of gastrointestinal hypomotility in clozapine tablets treated patients. Therefore, reassess bowel function frequently with careful attention to any changes in the frequency or character of bowel movements, as well as signs and symptoms of complications of hypomotility (e.g., nausea, vomiting, abdominal distension, abdominal pain). If constipation or gastrointestinal hypomotility are identified, monitor closely and treat promptly with appropriate laxatives, as necessary, to prevent severe complications. Consider prophylactic laxatives in high risk patients.

5.9 Eosinophilia

Eosinophilia, defined as a blood eosinophil count of greater than 700/μL, has occurred with clozapine tablets treatment. In clinical trials, approximately 1% of patients developed eosinophilia. Clozapine-related eosinophilia usually occurs during the first month of treatment. In some patients, it has been associated with myocarditis, pancreatitis, hepatitis, colitis, and nephritis. Such organ involvement could be consistent with a drug reaction with eosinophilia and systemic symptoms syndrome (DRESS), also known as drug induced hypersensitivity syndrome (DIHS). If eosinophilia develops during clozapine tablets treatment, evaluate promptly for signs and symptoms of systemic reactions, such as rash or other allergic symptoms, myocarditis, or other organ-specific disease associated with eosinophilia. If clozapine tablets-related systemic disease is suspected, discontinue clozapine tablets immediately.

If a cause of eosinophilia unrelated to clozapine tablets is identified (e.g., asthma, allergies, collagen vascular disease, parasitic infections, and specific neoplasms), treat the underlying cause and continue clozapine tablets.

Clozapine-related eosinophilia has also occurred in the absence of organ involvement and can resolve without intervention. There are reports of successful rechallenge after discontinuation of clozapine, without recurrence of eosinophilia. In the absence of organ involvement, continue clozapine tablets under careful monitoring. If the total eosinophil count continues to increase over several weeks in the absence of systemic disease, the decision to interrupt clozapine tablets therapy and rechallenge after the eosinophil count decreases should be based on the overall clinical assessment, in consultation with an internist or hematologist.

5.10 QT Interval Prolongation

QT prolongation, Torsades de Pointes and other life-threatening ventricular arrhythmias, cardiac arrest, and sudden death have occurred with clozapine tablets treatment. When prescribing clozapine tablets, consider the presence of additional risk factors for QT prolongation and serious cardiovascular reactions. Conditions that increase these risks include the following: history of QT prolongation, long QT syndrome, family history of long QT syndrome or sudden cardiac death, significant cardiac arrhythmia, recent myocardial infarction, uncompensated heart failure, treatment with other medications that cause QT prolongation, treatment with medications that inhibit the metabolism of clozapine, and electrolyte abnormalities.

Prior to initiating treatment with clozapine tablets, perform a careful physical examination, medical history, and concomitant medication history. Consider obtaining a baseline ECG and serum chemistry panel. Correct electrolyte abnormalities. Discontinue clozapine tablets if the QTcinterval exceeds 500 msec. If patients experience symptoms consistent with Torsades de Pointes, or other arrhythmias (e.g., syncope, presyncope, dizziness, or palpitations), obtain a cardiac evaluation and discontinue clozapine tablets.

Use caution when administering concomitant medications that prolong the QT interval or inhibit the metabolism of clozapine tablets. Drugs that cause QT prolongation include: specific antipsychotics (e.g., ziprasidone, iloperidone, chlorpromazine, thioridazine, mesoridazine, droperidol, pimozide), specific antibiotics (e.g., erythromycin, gatifloxacin, moxifloxacin, sparfloxacin), Class 1A antiarrhythmic medications (e.g., quinidine, procainamide) or Class III antiarrhythmics (e.g., amiodarone, sotalol), and others (e.g., pentamidine, levomethadyl acetate, methadone, halofantrine, mefloquine, dolasetron mesylate, probucol or tacrolimus). Clozapine is primarily metabolized by CYP isoenzymes 1A2, 2D6, and 3A4. Concomitant treatment with inhibitors of these enzymes can increase the concentration of clozapine tablets [see Drug Interactions (7.1)and Clinical Pharmacology (12.3)] .

Hypokalemia and hypomagnesemia increase the risk of QT prolongation. Hypokalemia can result from diuretic therapy, diarrhea, and other causes. Use caution when treating patients at risk for significant electrolyte disturbance, particularly hypokalemia. Obtain baseline measurements of serum potassium and magnesium levels, and periodically monitor electrolytes. Correct electrolyte abnormalities before initiating treatment with clozapine tablets.

5.11 Metabolic Changes

Atypical antipsychotic drugs, including clozapine tablets, have been associated with metabolic changes that can increase cardiovascular and cerebrovascular risk. These metabolic changes include hyperglycemia, dyslipidemia, and body weight gain. While atypical antipsychotic drugs may produce some metabolic changes, each drug in the class has its own specific risk profile.

Hyperglycemia and Diabetes Mellitus

Hyperglycemia, in some cases extreme and associated with ketoacidosis or hyperosmolar coma or death, has been reported in patients treated with atypical antipsychotics including clozapine tablets. Assessment of the relationship between atypical antipsychotic use and glucose abnormalities is complicated by the possibility of an increased background risk of diabetes mellitus in patients with schizophrenia and the increasing incidence of diabetes mellitus in the general population. Given these confounders, the relationship between atypical antipsychotic use and hyperglycemia-related adverse reactions is not completely understood. However, epidemiological studies suggest an increased risk of treatment-emergent, hyperglycemia-related adverse reactions in patients treated with the atypical antipsychotics. Precise risk estimates for hyperglycemia-related adverse reactions in patients treated with atypical antipsychotics are not available.

Patients with an established diagnosis of diabetes mellitus who are started on clozapine tablets should be monitored regularly for worsening of glucose control. Patients with risk factors for diabetes mellitus (e.g., obesity, family history of diabetes) who are starting treatment with atypical antipsychotics should undergo fasting blood glucose testing at the beginning of treatment and periodically during treatment. Any patient treated with atypical antipsychotics should be monitored for symptoms of hyperglycemia including polydipsia, polyuria, polyphagia, and weakness. Patients who develop symptoms of hyperglycemia during treatment with atypical antipsychotics should undergo fasting blood glucose testing. In some cases, hyperglycemia has resolved when the atypical antipsychotic was discontinued; however, some patients required continuation of antidiabetic treatment despite discontinuation of the suspect drug.

In a pooled data analysis of 8 studies in adult subjects with schizophrenia, the mean changes in fasting glucose concentration in the clozapine tablets and chlorpromazine groups were +11 mg/dL and +4 mg/dL respectively. A higher proportion of the clozapine tablets group demonstrated categorical increases from baseline in fasting glucose concentrations, compared to the chlorpromazine group (Table 4). The clozapine tablets doses were 100-900 mg per day (mean modal dose: 512 mg per day). The maximum chlorpromazine dose was 1800 mg per day (mean modal dose: 1029 mg per day). The median duration of exposure was 42 days for clozapine tablets and chlorpromazine.

Table 4. Categorical Changes in Fasting Glucose Level in Studies in Adult Subjects with Schizophrenia
Laboratory Parameter | Category Change (at least once) from baseline | Treatment Arm | N | n (%)
Fasting Glucose | Normal (< 100 mg/dL) to High (≥ 126 mg/dL) | Clozapine Tablets | 198 | 53 (27)
Fasting Glucose | Normal (< 100 mg/dL) to High (≥ 126 mg/dL) | Chlorpromazine | 135 | 14 (10)
Fasting Glucose | Borderline (100 mg/dL to 125 mg/dL) to High (≥ 126 mg/dL) | Clozapine Tablets | 57 | 24 (42)
Fasting Glucose | Borderline (100 mg/dL to 125 mg/dL) to High (≥ 126 mg/dL) | Chlorpromazine | 43 | 12 (28)

Dyslipidemia

Undesirable alterations in lipids have occurred in patients treated with atypical antipsychotics, including clozapine tablets. Clinical monitoring, including baseline and periodic follow-up lipid evaluations in patients using clozapine tablets, is recommended.

In a pooled data analysis of 10 studies in adult subjects with schizophrenia, clozapine tablets treatment was associated with increases in serum total cholesterol. No data were collected on LDL and HDL cholesterol. The mean increase in total cholesterol was 13 mg/dL in the clozapine tablets group and 15 mg/dL in the chlorpromazine group. In a pooled data analysis of 2 studies in adult subjects with schizophrenia, clozapine tablets treatment was associated with increases in fasting serum triglyceride. The mean increase in fasting triglyceride was 71 mg/dL (54%) in the clozapine tablets group and 39 mg/dL (35%) in the chlorpromazine group (Table 5). In addition, clozapine tablets treatment was associated with categorical increases in serum total cholesterol and triglyceride, as illustrated in Table 6. The proportion of patients with categorical increases in total cholesterol or fasting triglyceride increased with the duration of exposure. The median duration of clozapine tablets and chlorpromazine exposure was 45 days and 38 days, respectively. The clozapine tablets dose range was 100 mg to 900 mg daily; the maximum chlorpromazine dose was 1800 mg daily.

Table 5. Mean Changes in Total Cholesterol and Triglyceride Concentration in Studies in Adult Subjects with Schizophrenia
Treatment Arm | Baseline total cholesterol concentration (mg/dL) | Change from baseline mg/dL (%)
Clozapine Tablets (N = 334) | 184 | +13 (7)
Chlorpromazine (N = 185) | 182 | +15 (8)
 | Baseline triglyceride concentration (mg/dL) | Change from baseline mg/dL (%)
Clozapine Tablets (N = 6) | 130 | +71 (54)
Chlorpromazine (N = 7) | 110 | +39 (35)

Table 6. Categorical Changes in Lipid Concentrations in Studies in Adult Subjects with Schizophrenia
Laboratory Parameter | Category Change (at least once) from baseline | Treatment Arm | N | n (%)
Total Cholesterol (random or fasting) | Increase by ≥ 40 mg/dL | Clozapine Tablets | 334 | 111 (33)
Total Cholesterol (random or fasting) | Increase by ≥ 40 mg/dL | Chlorpromazine | 185 | 46 (25)
Total Cholesterol (random or fasting) | Normal (< 200 mg/dL) to High (≥ 240 mg/dL) | Clozapine Tablets | 222 | 18 (8)
Total Cholesterol (random or fasting) | Normal (< 200 mg/dL) to High (≥ 240 mg/dL) | Chlorpromazine | 132 | 3 (2)
Total Cholesterol (random or fasting) | Borderline (200 – 239 mg/dL) to High (≥ 240 mg/dL) | Clozapine Tablets | 79 | 30 (38)
Total Cholesterol (random or fasting) | Borderline (200 – 239 mg/dL) to High (≥ 240 mg/dL) | Chlorpromazine | 34 | 14 (41)
Triglycerides (fasting) | Increase by ≥ 50 mg/dL | Clozapine Tablets | 6 | 3 (50)
Triglycerides (fasting) | Increase by ≥ 50 mg/dL | Chlorpromazine | 7 | 3 (43)
Triglycerides (fasting) | Normal (< 150 mg/dL) to High (≥ 200 mg/dL) | Clozapine Tablets | 4 | 0 (0)
Triglycerides (fasting) | Normal (< 150 mg/dL) to High (≥ 200 mg/dL) | Chlorpromazine | 6 | 2 (33)
Triglycerides (fasting) | Borderline (≥ 150 mg/dL and < 200 mg/dL) to High (≥ 200 mg/dL) | Clozapine Tablets | 1 | 1 (100)
Triglycerides (fasting) | Borderline (≥ 150 mg/dL and < 200 mg/dL) to High (≥ 200 mg/dL) | Chlorpromazine | 1 | 0 (0)

Weight Gain

Weight gain has occurred with the use of antipsychotics, including clozapine tablets. Monitor weight during treatment with clozapine tablets. Table 7 summarizes the data on weight gain by the duration of exposure pooled from 11 studies with clozapine tablets and active comparators. The median duration of exposure was 609, 728, and 42 days, in the clozapine tablets, olanzapine, and chlorpromazine group, respectively.

Table 7. Mean Change in Body Weight (kg) by Duration of Exposure from Studies in Adult Subjects with Schizophrenia
Metabolic parameter | Exposure duration | Clozapine Tablets (N = 669) |  | Olanzapine (N = 442) |  | Chlorpromazine (N = 155)
Metabolic parameter | Exposure duration | n | Mean | n | Mean | n | Mean
Weight change from baseline | 2 weeks (Day 11-17) | 6 | +0.9 | 3 | +0.7 | 2 | -0.5
Weight change from baseline | 4 weeks (Day 21-35) | 23 | +0.7 | 8 | +0.8 | 17 | +0.6
Weight change from baseline | 8 weeks (Day 49-63) | 12 | +1.9 | 13 | +1.8 | 16 | +0.9
Weight change from baseline | 12 weeks (Day 70-98) | 17 | +2.8 | 5 | +3.1 | 0 | 0
Weight change from baseline | 24 weeks (Day 154-182) | 42 | -0.6 | 12 | +5.7 | 0 | 0
Weight change from baseline | 48 weeks (Day 322-350) | 3 | +3.7 | 3 | +13.7 | 0 | 0

Table 8 summarizes pooled data from 11 studies in adult subjects with schizophrenia demonstrating weight gain ≥ 7% of body weight relative to baseline. The median duration of exposure was 609, 728, and 42 days, in the clozapine tablets, olanzapine, and chlorpromazine group, respectively.

Table 8. Proportion of Adult Subjects in Schizophrenia Studies with Weight Gain ≥ 7% Relative to Baseline Body Weight
Weight change | Clozapine Tablets | Olanzapine | Chlorpromazine
N | 669 | 442 | 155
≥ 7% (inclusive) | 236 (35%) | 203 (46%) | 13 (8%)

5.12 Neuroleptic Malignant Syndrome

Antipsychotic drugs including clozapine tablets can cause a potentially fatal symptom complex referred to as Neuroleptic Malignant Syndrome (NMS). Clinical manifestations of NMS include hyperpyrexia, muscle rigidity, altered mental status, and autonomic instability (irregular pulse or blood pressure, tachycardia, diaphoresis, and cardiac dysrhythmias). Associated findings can include elevated creatine phosphokinase (CPK), myoglobinuria, rhabdomyolysis, and acute renal failure.

The diagnostic evaluation of patients with this syndrome is complicated. It is important to consider the presence of other serious medical conditions (e.g., severe neutropenia, infection, heat stroke, primary CNS pathology, central anticholinergic toxicity, extrapyramidal symptoms, and drug fever).

The management of NMS should include (1) immediate discontinuation of antipsychotic drugs and other drugs not essential to concurrent therapy, (2) intensive symptomatic treatment and medical monitoring, and (3) treatment of comorbid medical conditions. There is no general agreement about specific pharmacological treatments for NMS.

If a patient requires antipsychotic drug treatment after recovery from NMS, the potential reintroduction of drug therapy should be carefully considered. NMS can recur. Monitor closely if restarting treatment with antipsychotics.

NMS has occurred with clozapine tablets monotherapy and with concomitant CNS-active medications, including lithium.

5.13 Hepatotoxicity

Severe, life threatening, and in some cases fatal hepatotoxicity including hepatic failure, hepatic necrosis, and hepatitis have been reported in post marketing studies in patients treated with clozapine [see Adverse Reactions (6.2)] . Monitor for the appearance of signs and symptoms of hepatotoxicity such as fatigue, malaise, anorexia, nausea, jaundice, bilirubinemia, coagulopathy, and hepatic encephalopathy. Perform serum tests for liver injury and consider permanently discontinuing treatment if hepatitis or transaminase elevations combined with other systemic symptoms are due to clozapine.

5.14 Fever

During clozapine therapy, patients have experienced transient, clozapine-related fever. The peak incidence is within the first 3 weeks of treatment. While this fever is generally benign and self-limited, it may necessitate discontinuing treatment. The fever can be associated with an increase or decrease in WBC count. Carefully evaluate patients with fever to rule out severe neutropenia or infection. Consider the possibility of NMS [see Warnings and Precautions (5.11)] .

5.15 Pulmonary Embolism

Pulmonary embolism and deep-vein thrombosis have occurred in patients treated with clozapine tablets. Consider the possibility of pulmonary embolism in patients who present with deep-vein thrombosis, acute dyspnea, chest pain, or with other respiratory signs and symptoms. Whether pulmonary embolus and deep-vein thrombosis can be attributed to clozapine or some characteristic(s) of patients is not clear.

5.16 Anticholinergic Toxicity

Clozapine tablets have potent anticholinergic effects. Treatment with clozapine tablets can result in CNS and peripheral anticholinergic toxicity, especially at higher dosages, or in overdose situations [see Overdosage (10)] . Use with caution in patients with a current diagnosis or prior history of constipation, urinary retention, clinically significant prostatic hypertrophy, or other conditions in which anticholinergic effects can lead to significant adverse reactions. When possible, avoid concomitant use, with other anticholinergic medications because the risk for anticholinergic toxicity or severe gastrointestinal adverse reactions is increased [see Warnings and Precautions (5.8), Drug Interactions (7.1)] .

5.17 Interference with Cognitive and Motor Performance

Clozapine tablets can cause sedation and impairment of cognitive and motor performance. Caution patients about operating hazardous machinery, including automobiles, until they are reasonably certain that clozapine tablets do not affect them adversely. These reactions may be dose-related. Consider reducing the dose if they occur.

5.18 Tardive Dyskinesia

Tardive dyskinesia (TD) has occurred in patients treated with antipsychotic drugs, including clozapine tablets. The syndrome consists of potentially irreversible, involuntary, dyskinetic movements. The risk of TD and the likelihood that it will become irreversible are believed to increase with greater durations of treatment and higher total cumulative doses. However, the syndrome can develop after relatively brief treatment periods at low doses. Prescribe clozapine tablets in a manner that is most likely to minimize the risk of developing TD. Use the lowest effective dose and the shortest duration necessary to control symptoms. Periodically assess the need for continued treatment. Consider discontinuing treatment if TD occurs. However, some patients may require treatment with clozapine tablets despite the presence of the syndrome.

There is no known treatment for TD. However, the syndrome may remit partially or completely if treatment is discontinued. Antipsychotic treatment, itself, may suppress (or partially suppress) the signs and symptoms, and it has the potential to mask the underlying process. The effect of symptom suppression on the long-term course of TD is unknown.

5.19 Cerebrovascular Adverse Reactions

In controlled trials, elderly patients with dementia-related psychosis treated with some atypical antipsychotics had an increased risk (compared to placebo) of cerebrovascular adverse reactions (e.g., stroke, transient ischemic attack), including fatalities. The mechanism for this increased risk is not known. An increased risk cannot be excluded for clozapine tablets or other antipsychotics or other patient populations. Clozapine tablets should be used with caution in patients with risk factors for cerebrovascular adverse reactions.

5.20 Recurrence of Psychosis and Cholinergic Rebound after Abrupt Discontinuation of Clozapine Tablets

If abrupt discontinuation of clozapine tablets is necessary (because of severe neutropenia or another medical condition, for example) [see Dosage and Administration (2.4), Warnings and Precautions (5.1)] , monitor carefully for the recurrence of psychotic symptoms and adverse reactions related to cholinergic rebound, such as profuse sweating, headache, nausea, vomiting and diarrhea.

6 ADVERSE REACTIONS

The following adverse reactions are discussed in more detail in other sections of the labeling:

- Severe Neutropenia [see Warnings and Precautions (5.1)]
- Orthostatic Hypotension, Bradycardia, and Syncope [see Warnings and Precautions (5.3)]
- Falls [see Warnings and Precautions (5.4)]
- Seizures [see Warnings and Precautions (5.5)]
- Myocarditis, Pericarditis, Cardiomyopathy, and Mitral Valve Incompetence [see Warnings and Precautions (5.6)]
- Increased Mortality in Elderly Patients with Dementia-Related Psychosis [see Warnings and Precautions (5.7)]
- Gastrointestinal Hypomotility with Severe Complications [see Warnings and Precautions (5.8)]
- Eosinophilia [see Warnings and Precautions (5.9)]
- QT Interval Prolongation [see Warnings and Precautions (5.10)]
- Metabolic Changes (Hyperglycemia and Diabetes Mellitus, Dyslipidemia, and Weight Gain) [see Warnings and Precautions (5.11)]
- Neuroleptic Malignant Syndrome [see Warnings and Precautions (5.12)]
- Hepatotoxicity [see Warnings and Precautions (5.13)]
- Fever [see Warnings and Precautions (5.14)]
- Pulmonary Embolism [see Warnings and Precautions (5.15)]
- Anticholinergic Toxicity [see Warnings and Precautions (5.16)]
- Interference with Cognitive and Motor Performance [see Warnings and Precautions (5.17)]
- Tardive Dyskinesia [see Warnings and Precautions (5.18)]
- Cerebrovascular Adverse Reactions [see Warnings and Precautions (5.19)]
- Recurrence of Psychosis and Cholinergic Rebound after Abrupt Discontinuation [see Warnings and Precautions (5.20)]

6.1 Clinical Trials Experience

Because clinical trials are conducted under widely varying conditions, adverse reaction rates observed in the clinical trials of a drug cannot be directly compared to rates in the clinical trials of another drug and may not reflect the rates observed in clinical practice.

The most commonly reported adverse reactions (≥ 5%) across clozapine tablets clinical trials were: CNS reactions, including sedation, dizziness/vertigo, headache, and tremor; cardiovascular reactions, including tachycardia, hypotension, and syncope; autonomic nervous system reactions, including hypersalivation, sweating, dry mouth, and visual disturbances; gastrointestinal reactions, including constipation and nausea; and fever. Table 9 summarizes the most commonly reported adverse reactions (≥ 5%) in clozapine tablets-treated patients (compared to chlorpromazine-treated patients) in the pivotal, 6-week, controlled trial in treatment-resistant schizophrenia.

Table 9. Common Adverse Reactions (≥ 5%) in the 6-Week, Randomized, Chlorpromazine-Controlled Trial in Treatment-Resistant Schizophrenia
Adverse Reaction | Clozapine Tablets (N = 126) (%) | Chlorpromazine (N = 142) (%)
Sedation | 21 | 13
Tachycardia | 17 | 11
Constipation | 16 | 12
Dizziness | 14 | 16
Hypotension | 13 | 38
Fever (hyperthermia) | 13 | 4
Hypersalivation | 13 | 1
Hypertension | 12 | 5
Headache | 10 | 10
Nausea/vomiting | 10 | 12
Dry mouth | 5 | 20

Table 10 summarizes the adverse reactions reported in clozapine tablets-treated patients at a frequency of 2% or greater across all clozapine tablets studies (excluding the 2-year InterSePT™ Study). These rates are not adjusted for duration of exposure.

Table 10. Adverse Reactions (≥ 2%) Reported in Clozapine Tablets-Treated Patients (N = 842) Across all Clozapine Tablets Studies (excluding the 2-year InterSePT™ Study)
Body System; Adverse Reaction [Rate based on population of approximately 1700 exposed during premarket clinical evaluation of clozapine tablets.] | Clozapine Tablets N = 842 Percentage of Patients
Central Nervous System
Drowsiness/Sedation | 39
Dizziness/Vertigo | 19
Headache | 7
Tremor | 6
Syncope | 6
Disturbed Sleep/Nightmares | 4
Restlessness | 4
Hypokinesia/Akinesia | 4
Agitation | 4
Seizures (convulsions) | 3
Rigidity | 3
Akathisia | 3
Confusion | 3
Fatigue | 2
Insomnia | 2
Cardiovascular
Tachycardia | 25
Hypotension | 9
Hypertension | 4
Gastrointestinal
Constipation | 14
Nausea | 5
Abdominal Discomfort/Heartburn | 4
Nausea/Vomiting | 3
Vomiting | 3
Diarrhea | 2
Urogenital
Urinary Abnormalities | 2
Autonomic Nervous System
Salivation | 31
Sweating | 6
Dry Mouth | 6
Visual Disturbances | 5
Skin
Rash | 2
Hemic/Lymphatic
Leukopenia/Decreased WBC/Neutropenia | 3
Miscellaneous
Fever | 5
Weight Gain | 4

Table 11 summarizes the most commonly reported adverse reactions (≥ 10% of the clozapine tablets or olanzapine group) in the InterSePT™ Study. This was an adequate and well-controlled, two-year study evaluating the efficacy of clozapine tablets relative to olanzapine in reducing the risk of suicidal behavior in patients with schizophrenia or schizoaffective disorder. The rates are not adjusted for duration of exposure.

Table 11. Incidence of Adverse Reactions in Patients Treated with Clozapine Tablets or Olanzapine in the InterSePT™ Study (≥ 10% in the Clozapine Tablets or Olanzapine Group)
Adverse Reactions | Clozapine Tablets N = 479 % Reporting | Olanzapine N = 477 % Reporting
Salivary hypersecretion | 48 | 6
Somnolence | 46 | 25
Weight increased | 31 | 56
Dizziness (excluding vertigo) | 27 | 12
Constipation | 25 | 10
Insomnia | 20 | 33
Nausea | 17 | 10
Vomiting | 17 | 9
Dyspepsia | 14 | 8

Dystonia

Class Effect

Symptoms of dystonia, prolonged abnormal contractions of muscle groups, may occur in susceptible individuals during the first few days of treatment. Dystonic symptoms include: spasm of the neck muscles, sometimes progressing to tightness of the throat, swallowing difficulty, difficulty breathing, and/or protrusion of the tongue. While these symptoms can occur at low doses, they occur more frequently and with greater severity with high potency and at higher doses of first generation antipsychotic drugs. An elevated risk of acute dystonia is observed in males and younger age groups.

6.2 Postmarketing Experience

The following adverse reactions have been identified during post-approval use of clozapine. Because these reactions are reported voluntarily from a population of uncertain size, it is not always possible to reliably estimate their frequency or establish a causal relationship to drug exposure.

Central Nervous System

Delirium, EEG abnormal, myoclonus, paresthesia, possible cataplexy, status epilepticus, obsessive compulsive symptoms, restless leg syndrome and post-discontinuation cholinergic rebound adverse reactions.

Cardiovascular System

Atrial or ventricular fibrillation, ventricular tachycardia, palpitations, QT interval prolongation, Torsades de Pointes, mitral valve incompetence associated with clozapine-related cardiomyopathy, myocardial infarction, cardiac arrest, myocarditis, pericarditis, and periorbital edema.

Endocrine System

Pseudopheochromocytoma

Gastrointestinal System

Acute pancreatitis, dysphagia, salivary gland swelling, colitis, megacolon, fecal incontinence, and intestinal ischemia, infarction, perforation, ulceration or necrosis.

Hepatobiliary System

Cholestasis, hepatitis, jaundice, hepatotoxicity, hepatic steatosis, hepatic necrosis, hepatic fibrosis, hepatic cirrhosis, liver injury (hepatic, cholestatic, and mixed), and liver failure.

Immune System Disorders

Angioedema, leukocytoclastic vasculitis.

Urogenital System

Acute interstitial nephritis, nocturnal enuresis, priapism, renal failure, and retrograde ejaculation.

Skin and Subcutaneous Tissue Disorders

Hypersensitivity reactions: photosensitivity, vasculitis, erythema multiforme, skin pigmentation disorder, and Stevens-Johnson Syndrome.

Musculoskeletal System and Connective Tissue Disorders

Myasthenic syndrome, rhabdomyolysis, and systemic lupus erythematosus.

Respiratory System

Aspiration, pleural effusion, pneumonia, lower respiratory tract infection, sleep apnea.

Hemic and Lymphatic System

Mild, moderate, or severe leukopenia, agranulocytosis, granulocytopenia, WBC decreased, deep-vein thrombosis, elevated hemoglobin/hematocrit, erythrocyte sedimentation rate (ESR) increased, sepsis, thrombocytosis, and thrombocytopenia.

Vision Disorders

Narrow-angle glaucoma.

Miscellaneous

Creatine phosphokinase elevation, hyperuricemia, hyponatremia, polyserositis, and weight loss.

7 DRUG INTERACTIONS

7.1 Potential for Other Drugs to Affect Clozapine Tablets

Clozapine is a substrate for many cytochrome P450 isozymes, in particular CYP1A2, CYP3A4, and CYP2D6. Use caution when administering clozapine tablets concomitantly with drugs that are inducers or inhibitors of these enzymes.

CYP1A2 Inhibitors

Concomitant use of clozapine tablets and CYP1A2 inhibitors can increase plasma levels of clozapine, potentially resulting in adverse reactions. Reduce the clozapine tablets dose to one-third of the original dose when clozapine tablets are coadministered with strong CYP1A2 inhibitors (e.g., fluvoxamine, ciprofloxacin, or enoxacin). The clozapine tablets dose should be increased to the original dose when coadministration of strong CYP1A2 inhibitors is discontinued [see Dosage and Administration (2.6), Clinical Pharmacology (12.3)] .

Moderate or weak CYP1A2 inhibitors include oral contraceptives and caffeine. Monitor patients closely when clozapine tablets are coadministered with these inhibitors. Consider reducing the clozapine tablets dosage if necessary [see Dosage and Administration (2.6)] .

CYP2D6 and CYP3A4 Inhibitors

Concomitant treatment with clozapine tablets and CYP2D6 or CYP3A4 inhibitors (e.g., cimetidine, escitalopram, erythromycin, paroxetine, bupropion, fluoxetine, quinidine, duloxetine, terbinafine, or sertraline) can increase clozapine levels and lead to adverse reactions [see Clinical Pharmacology (12.3)] . Use caution and monitor patients closely when using such inhibitors. Consider reducing the clozapine tablets dose [see Dosage and Administration (2.6)] .

CYP1A2 and CYP3A4 Inducers

Concomitant treatment with drugs that induce CYP1A2 or CYP3A4 can decrease the plasma concentration of clozapine, resulting in decreased effectiveness of clozapine tablets. Tobacco smoke is a moderate inducer of CYP1A2. Strong CYP3A4 inducers include carbamazepine, phenytoin, St. John’s wort, and rifampin. It may be necessary to increase the clozapine tablets dose if used concomitantly with inducers of these enzymes. However, concomitant use of clozapine tablets and strong CYP3A4 inducers is not recommended [see Dosage and Administration (2.6)] .

Consider reducing the clozapine tablets dosage when discontinuing coadministered enzyme inducers; because discontinuation of inducers can result in increased clozapine plasma levels and an increased risk of adverse reactions [see Dosage and Administration (2.6)] .

Anticholinergic Drugs

Concomitant treatment with clozapine and other drugs with anticholinergic activity (e.g., benztropine, cyclobenzaprine, diphenhydramine) can increase the risk for anticholinergic toxicity and severe gastrointestinal adverse reactions related to hypomotility. Avoid concomitant use of clozapine tablets with anticholinergic drugs when possible [see Warnings and Precautions (5.8, 5.16)].

Drugs that Cause QT Interval Prolongation

Use caution when administering concomitant medications that prolong the QT interval or inhibit the metabolism of clozapine. Drugs that cause QT prolongation include: specific antipsychotics (e.g., ziprasidone, iloperidone, chlorpromazine, thioridazine, mesoridazine, droperidol, and pimozide), specific antibiotics (e.g., erythromycin, gatifloxacin, moxifloxacin, sparfloxacin), Class 1A antiarrhythmics (e.g., quinidine, procainamide) or Class III antiarrhythmics (e.g., amiodarone, sotalol), and others (e.g., pentamidine, levomethadyl acetate, methadone, halofantrine, mefloquine, dolasetron mesylate, probucol or tacrolimus) [see Warnings and Precautions (5.10)] .

7.2 Potential for Clozapine Tablets to Affect Other Drugs

Concomitant use of clozapine tablets with other drugs metabolized by CYP2D6 can increase levels of these CYP2D6 substrates. Use caution when coadministering clozapine tablets with other drugs that are metabolized by CYP2D6. It may be necessary to use lower doses of such drugs than usually prescribed. Such drugs include specific antidepressants, phenothiazines, carbamazepine, and Type 1C antiarrhythmics (e.g., propafenone, flecainide, and encainide).

8 USE IN SPECIFIC POPULATIONS

8.1 Pregnancy

Pregnancy Exposure Registry

There is a pregnancy exposure registry that monitors pregnancy outcomes in women exposed to atypical antipsychotics, including clozapine tablets, during pregnancy. Healthcare providers are encouraged to advise patients to register by calling the National Pregnancy Registry for Atypical Antipsychotics at 1-866-961-2388 or visiting http://womensmentalhealth.org/clinical-and-research-programs/pregnancyregistry/.

Risk Summary

Neonates exposed to antipsychotic drugs, including clozapine tablets, during the third trimester are at risk for extrapyramidal and/or withdrawal symptoms following delivery (see Clinical Considerations). Available data from published epidemiologic studies over decades of use with clozapine during pregnancy have not established a drug-associated risk of major birth defects, miscarriage, or adverse maternal or fetal outcomes (see Data). There are risks to the mother associated with untreated schizophrenia and with exposure to antipsychotics, including clozapine tablets, during pregnancy (see Clinical Considerations).

In animal reproduction studies, no adverse developmental effects were observed when clozapine was administered orally to pregnant rats or rabbits during the period of organogenesis, or to pregnant rats during pregnancy and lactation, at doses up to approximately 0.4 and 0.9 times the maximum recommended human dose (MRHD) of 900 mg/day, for rats and rabbits respectively, based on mg/m2 body surface area (see Data).

The background risk of major birth defects and miscarriage for the indicated populations is unknown. All pregnancies have a background risk of birth defects, loss, or other adverse outcomes. In the U.S. general population, the estimated background risk of major birth defects and miscarriage in clinically recognized pregnancies is 2 to 4% and 15 to 20%, respectively.

Clinical Considerations

Disease-associated maternal and/or embryo/fetal risk

There is a risk to the mother from untreated schizophrenia, including increased risk of relapse, hospitalization, and suicide. Schizophrenia is associated with increased adverse perinatal outcomes, including preterm birth. It is not known if this is a direct result of the illness or other comorbid factors.

Fetal/Neonatal adverse reactions

Extrapyramidal and/or withdrawal symptoms, including agitation, hypertonia, hypotonia, tremor, somnolence, respiratory distress, and feeding disorder have been reported in neonates who have been exposed to antipsychotic drugs, including clozapine tablets, during the third trimester of pregnancy. These symptoms have varied in severity. Monitor neonates for extrapyramidal and/or withdrawal symptoms and manage symptoms appropriately. Some neonates recovered within hours or days without specific treatment; others required prolonged hospitalization.

Data

Animal Data

In embryofetal developmental studies, clozapine had no effects on maternal parameters, litter sizes, or fetal parameters when administered orally to pregnant rats and rabbits during the period of organogenesis at doses up to 0.4 and 0.9 times, respectively, the MRHD of 900 mg/day on a mg/m2 body surface area basis.

In peri/postnatal developmental studies, pregnant female rats were administered clozapine over the last third of pregnancy and until day 21 postpartum. Observations were made on fetuses at birth and during the postnatal period; the offspring were allowed to reach sexual maturity and mated. Clozapine caused a decrease in maternal body weight but had no effects on litter size or body weights of either F1 or F2 generations at doses up to 0.4 times the MRHD of 900 mg/day on a mg/m2 body surface area basis.

8.2 Lactation

Risk Summary

Clozapine is present in human milk. There is one case report of sedation and a report of agranulocytosis in an infant exposed to clozapine through human milk (see Clinical Considerations). There is no information on the effects of clozapine on milk production. The developmental and health benefits of breastfeeding should be considered along with the mother’s clinical need for clozapine tablets and any potential adverse effects on the breastfed child from clozapine tablets or from the underlying maternal condition.

Clinical Considerations

Infants exposed to clozapine tablets should be monitored for excess sedation and neutropenia.

8.4 Pediatric Use

Safety and effectiveness in pediatric patients have not been established.

8.5 Geriatric Use

There have not been sufficient numbers of geriatric patients in clinical studies utilizing clozapine tablets to determine whether those over 65 years of age differ from younger subjects in their response to clozapine tablets.

Orthostatic hypotension and tachycardia can occur with clozapine tablets treatment [see Boxed Warningand Warnings and Precautions (5.3)] . Elderly patients, particularly those with compromised cardiovascular functioning, may be more susceptible to these effects.

Elderly patients may be particularly susceptible to the anticholinergic effects of clozapine tablets, such as urinary retention and constipation [see Warnings and Precautions (5.16)] .

Carefully select clozapine tablets doses in elderly patients, taking into consideration their greater frequency of decreased hepatic, renal, or cardiac function, as well as other concomitant disease and other drug therapy. Clinical experience suggests that the prevalence of tardive dyskinesia appears to be highest among the elderly; especially elderly women [see Warnings and Precautions (5.18)] .

8.6 Patients with Renal or Hepatic Impairment

Dose reduction may be necessary in patients with significant impairment of renal or hepatic function. Clozapine concentrations may be increased in these patients, because clozapine is almost completely metabolized and then excreted [see Dosage and Administration (2.7), Clinical Pharmacology (12.3)] .

8.7 CYP2D6 Poor Metabolizers

Dose reduction may be necessary in patients who are CYP2D6 poor metabolizers. Clozapine concentrations may be increased in these patients, because clozapine is almost completely metabolized and then excreted [see Dosage and Administration (2.7), Clinical Pharmacology (12.3)] .

8.8 Hospice Patients

For hospice patients (i.e., terminally ill patients with an estimated life expectancy of six months or less), the prescriber may reduce the ANC monitoring frequency to once every 6 months, after a discussion with the patient and his/her caregiver. Individual treatment decisions should weigh the importance of monitoring ANC in the context of the need to control psychiatric symptoms and the patient’s terminal illness.

10 OVERDOSAGE

10.1 Overdosage Experience

The most commonly reported signs and symptoms associated with clozapine overdose are: sedation, delirium, coma, tachycardia, hypotension, respiratory depression or failure; and hypersalivation. There are reports of aspiration pneumonia, cardiac arrhythmias, and seizure. Fatal overdoses have been reported with clozapine, generally at doses above 2500 mg. There have also been reports of patients recovering from overdoses well in excess of 4 g.

10.2 Management of Overdosage

There is no available specific antidote to an overdose of clozapine tablets. Establish and maintain an airway; ensure adequate oxygenation and ventilation. Monitor cardiac status and vital signs. Use general symptomatic and supportive measures. Consider the possibility of multiple-drug involvement.

Contact a Certified Poison Control Center for the most up to date information on the management of overdosage (1-800-222-1222).

11 DESCRIPTION

Clozapine, an atypical antipsychotic drug, is a tricyclic dibenzodiazepine derivative, 8-Chloro-11-(4-methyl-1-piperazinyl)-5 H-dibenzo [ b,e] [1,4] diazepine. The structural formula is:

Clozapine is available in peach tablets of 25 mg or green tablets of 50 mg, 100 mg or 200 mg for oral administration.

Active Ingredient: clozapine

Inactive ingredients are colloidal silicon dioxide, crospovidone, lactose monohydrate, magnesium stearate, microcrystalline cellulose, and sodium lauryl sulfate. In addition, the 25 mg tablets contain FD&C Red No. 40 Aluminum Lake, and the 50 mg, 100 mg and 200 mg tablets contain FD&C Blue No. 2 Aluminum Lake.

12 CLINICAL PHARMACOLOGY

12.1 Mechanism of Action

The mechanism of action of clozapine is unknown. However, it has been proposed that the therapeutic efficacy of clozapine in schizophrenia is mediated through antagonism of the dopamine type 2 (D2) and the serotonin type 2A (5-HT2A) receptors. Clozapine also acts as an antagonist at adrenergic, cholinergic, histaminergic and other dopaminergic and serotonergic receptors.

12.2 Pharmacodynamics

Clozapine demonstrated binding affinity to the following receptors: histamine H1(Ki1.1 nM), adrenergic α1A(Ki1.6 nM), serotonin 5-HT6(Ki4 nM), serotonin 5-HT2A(Ki5.4 nM), muscarinic M1(Ki6.2 nM), serotonin 5-HT7(Ki6.3 nM), serotonin 5-HT2C(Ki9.4 nM), dopamine D4(Ki24 nM), adrenergic α2A(Ki90 nM), serotonin 5-HT3(Ki95 nM), serotonin 5-HT1A(Ki120 nM), dopamine D2(Ki160 nM), dopamine D1(Ki270 nM), dopamine D5(Ki454 nM), and dopamine D3(Ki555 nM).

Clozapine causes little or no prolactin elevation.

Clinical electroencephalogram (EEG) studies demonstrated that clozapine increases delta and theta activity and slows dominant alpha frequencies. Enhanced synchronization occurs. Sharp wave activity and spike and wave complexes may also develop. Patients have reported an intensification of dream activity during clozapine therapy. REM sleep was found to be increased to 85% of the total sleep time. In these patients, the onset of REM sleep occurred almost immediately after falling asleep.

12.3 Pharmacokinetics

Absorption

In humans, clozapine tablets (25 mg and 100 mg) are equally bioavailable relative to a clozapine solution. Following oral administration of clozapine tablets 100 mg twice daily, the average steady-state peak plasma concentration was 319 ng/mL (range: 102 to 771 ng/mL), occurring at the average of 2.5 hours (range: 1 to 6 hours) after dosing. The average minimum concentration at steady-state was 122 ng/mL (range: 41 to 343 ng/mL), after 100 mg twice daily dosing. Food does not appear to affect the systemic bioavailability of clozapine tablets. Thus, clozapine tablets may be administered with or without food.

Distribution

Clozapine is approximately 97% bound to serum proteins. The interaction between clozapine and other highly protein-bound drugs has not been fully evaluated but may be important [see Drug Interactions (7)] .

Metabolism and Excretion

Clozapine is almost completely metabolized prior to excretion, and only trace amounts of unchanged drug are detected in the urine and feces. Clozapine is a substrate for many cytochrome P450 isozymes, in particular CYP1A2, CYP2D6, and CYP3A4. Approximately 50% of the administered dose is excreted in the urine and 30% in the feces. The demethylated, hydroxylated, and N-oxide derivatives are components in both urine and feces. Pharmacological testing has shown the desmethyl metabolite (norclozapine) to have only limited activity, while the hydroxylated and N-oxide derivatives were inactive. The mean elimination half-life of clozapine after a single 75 mg dose was 8 hours (range: 4 to 12 hours), compared to a mean elimination half-life of 12 hours (range: 4 to 66 hours), after achieving steady-state with 100 mg twice daily dosing.

A comparison of single-dose and multiple-dose administration of clozapine demonstrated that the elimination half-life increased significantly after multiple dosing relative to that after single-dose administration, suggesting the possibility of concentration-dependent pharmacokinetics. However, at steady-state, approximately dose-proportional changes with respect to AUC (area under the curve), peak, and minimum clozapine plasma concentrations were observed after administration of 37.5, 75, and 150 mg twice daily.

Drug-Drug Interaction Studies

Fluvoxamine

A pharmacokinetic study was conducted in 16 schizophrenic patients who received clozapine under steady-state conditions. After coadministration of fluvoxamine for 14 days, mean trough concentrations of clozapine and its metabolites, N-desmethylclozapine and clozapine N-oxide, were elevated about three-fold compared to baseline steady-state concentrations.

Paroxetine, Fluoxetine, and Sertraline

In a study of schizophrenic patients (n = 14) who received clozapine under steady-state conditions, coadministration of paroxetine produced only minor changes in the levels of clozapine and its metabolites. However, other published reports describe modest elevations (less than two-fold) of clozapine and metabolite concentrations when clozapine was taken with paroxetine, fluoxetine, and sertraline.

Specific Population Studies

Renal or Hepatic Impairment

No specific pharmacokinetic studies were conducted to investigate the effects of renal or hepatic impairment on the pharmacokinetics of clozapine. Higher clozapine plasma concentrations are likely in patients with significant renal or hepatic impairment when given usual doses.

CYP2D6 Poor Metabolizers

A subset (3%-10%) of the population has reduced activity of CYP2D6 (CYP2D6 poor metabolizers). These individuals may develop higher than expected plasma concentrations of clozapine when given usual doses.

Patients with Pneumonia and other Inflammatory Conditions

Published case reports describe examples where pneumonia or other inflammatory conditions may increase clozapine concentrations. The clinical significance, the impact of treatments to modulate this inflammation, and mechanism of this potential increase in clozapine concentrations have not been fully characterized but may involve reduced cytochrome P450 1A2 activity.

13 NONCLINICAL TOXICOLOGY

13.1 Carcinogenesis, Mutagenesis, Impairment of Fertility

Carcinogenesis

No carcinogenic potential was demonstrated in long-term studies in mice and rats at doses up to 0.3 times and 0.4 times, respectively, the maximum recommended human dose (MRHD) of 900 mg/day on a mg/m^2body surface area basis.

Mutagenesis

Clozapine was not genotoxic when tested in the following gene mutation and chromosomal aberration tests: the bacterial Ames test, the in vitromammalian V79 in Chinese hamster cells, the in vitrounscheduled DNA synthesis in rat hepatocytes or the in vivomicronucleus assay in mice.

Impairment of Fertility

Clozapine had no effect on any parameters of fertility, pregnancy, fetal weight or postnatal development when administered orally to male rats 70 days before mating and to female rats for 14 days before mating at doses up to 0.4 times the MRHD of 900 mg/day on a mg/m^2body surface area basis.

14 CLINICAL STUDIES

14.1 Treatment-Resistant Schizophrenia

The efficacy of clozapine tablets in treatment-resistant schizophrenia was established in a multicenter, randomized, double-blind, active-controlled (chlorpromazine) study in patients with a DSM-III diagnosis of schizophrenia who had inadequate responses to at least 3 different antipsychotics (from at least 2 different chemical classes) during the preceding 5 years. The antipsychotic trials must have been judged adequate; the antipsychotic dosages must have been equivalent to or greater than 1000 mg per day of chlorpromazine for a period of at least 6 weeks, each without significant reduction of symptoms. There must have been no period of good functioning within the preceding 5 years. Patients must have had a baseline score of at least 45 on the investigator-rated Brief Psychiatric Rating Scale (BPRS). On the 18-item BPRS, 1 indicates the absence of symptoms, and 7 indicates severe symptoms; the maximum potential total BPRS score is 126. At baseline, the mean BPRS score was 61. In addition, patients must have had a score of at least 4 on at least two of the following four individual BPRS items: conceptual disorganization, suspiciousness, hallucinatory behavior, and unusual thought content. Patients must have had a Clinical Global Impressions–Severity Scale score of at least 4 (moderately ill).

In the prospective, lead-in phase of the trial, all patients (N = 305) initially received single-blind treatment with haloperidol (the mean dose was 61 mg per day) for 6 weeks. More than 80% of patients completed the 6-week trial. Patients with an inadequate response to haloperidol (N = 268) were randomized to double-blind treatment with clozapine tablets (N = 126) or chlorpromazine (N = 142). The maximum daily clozapine tablets dose was 900 mg; the mean daily dose was > 600 mg. The maximum daily chlorpromazine dose was 1800 mg; the mean daily dose was > 1200 mg.

The primary endpoint was treatment response, predefined as a decrease in BPRS score of at least 20% and either (1) a CGI-S score of ≤ 3 (mildly ill), or (2) a BPRS score of ≤ 35, at the end of 6 weeks of treatment. Approximately 88% of patients from the clozapine tablets and chlorpromazine groups completed the 6-week trial. At the end of 6 weeks, 30% of the clozapine tablets group responded to treatment, and 4% of the chlorpromazine group responded to treatment. The difference was statistically significant (p < 0.001). The mean change in total BPRS score was -16 and -5 in the clozapine tablets and chlorpromazine group, respectively; the mean change in the 4 key BPRS item scores was -5 and -2 in the clozapine tablets and chlorpromazine group, respectively; and the mean change in CGI-S score was -1.2 and -0.4, in the clozapine tablets and chlorpromazine group, respectively. These changes in the clozapine tablets group were statistically significantly greater than in the chlorpromazine group (p < 0.001 in each analysis).

14.2 Recurrent Suicidal Behavior in Schizophrenia or Schizoaffective Disorder

The effectiveness of clozapine tablets in reducing the risk of recurrent suicidal behavior was assessed in the International Suicide Prevention Trial (InterSePT™, a trademark of Novartis Pharmaceuticals Corporation). This was a prospective, randomized, open-label, active-controlled, multicenter, international, parallel-group comparison of clozapine tablets versus olanzapine (Zyprexa®, a registered trademark of Eli Lilly and Company) in 956 patients with schizophrenia or schizoaffective disorder (DSM-IV) who were judged to be at risk for recurrent suicidal behavior. Only about one-fourth of these patients (27%) were considered resistant to standard antipsychotic drug treatment. To enter the trial, patients must have met 1 of the following criteria:

- They had attempted suicide within the three years prior to their baseline evaluation.
- They had been hospitalized to prevent a suicide attempt within the three years prior to their baseline evaluation.
- They demonstrated moderate-to-severe suicidal ideation with a depressive component within one week prior to their baseline evaluation.
- They demonstrated moderate-to-severe suicidal ideation accompanied by command hallucinations to do self-harm within one week prior to their baseline evaluation.

Dosing regimens for each treatment group were determined by individual investigators and were individualized by patient. Dosing was flexible, with a dose range of 200-900 mg/day for clozapine tablets and 5-20 mg/day for olanzapine. For the 956 patients who received clozapine tablets or olanzapine in this study, there was extensive use of concomitant psychotropics: 84% with antipsychotics, 65% with anxiolytics, 53% with antidepressants, and 28% with mood stabilizers. There was significantly greater use of concomitant psychotropic medications among the patients in the olanzapine group.

The primary efficacy measure was time to (1) a significant suicide attempt, including a completed suicide; (2) hospitalization due to imminent suicide risk, including increased level of surveillance for suicidality for patients already hospitalized; or (3) worsening of suicidality severity as demonstrated by “much worsening” or “very much worsening” from baseline in the Clinical Global Impression of Severity of Suicidality as assessed by the Blinded Psychiatrist (CGI-SS-BP) scale. A determination of whether or not a reported event met criterion 1 or 2 above was made by the Suicide Monitoring Board (SMB), a group of experts blinded to patient data.

A total of 980 patients were randomized to the study and 956 received study medication. Sixty-two percent of the patients were diagnosed with schizophrenia, and the remainder (38%) were diagnosed with schizoaffective disorder. Only about one-fourth of the total patient population (27%) was identified as “treatment-resistant” at baseline. There were more males than females in the study (61% of all patients were male). The mean age of patients entering the study was 37 years of age (range 18-69). Most patients were Caucasian (71%), 15% were Black, 1% were Asian, and 13% were classified as being of “other” races.

Patients treated with clozapine tablets had a statistically significant longer delay in the time to recurrent suicidal behavior in comparison with olanzapine. This result should be interpreted only as evidence of the effectiveness of clozapine tablets in delaying time to recurrent suicidal behavior and not a demonstration of the superior efficacy of clozapine tablets over olanzapine.

The probability of experiencing (1) a significant suicide attempt, including a completed suicide, or (2) hospitalization because of imminent suicide risk, including increased level of surveillance for suicidality for patients already hospitalized, was lower for clozapine tablets patients than for olanzapine patients at Week 104: clozapine tablets 24% versus olanzapine 32%; 95% CI of the difference: 2%, 14% (Figure 1).

16 HOW SUPPLIED/STORAGE AND HANDLING

16.1 How Supplied

Clozapine Tablets, USP are available containing 25 mg, 100 mg or 200 mg of clozapine, USP.

The 25 mg tablets are peach, round, functionally scored tablets debossed with Cto the left of the score and 7to the right of the score on one side of the tablet and Mon the other side. They are available as follows:

NDC 51079-921-20 – Unit dose blister packages of 100 (10 cards of 10 tablets each).

The 100 mg tablets are green, round, functionally scored tablets debossed with C11above the score and blank below the score on one side of the tablet and Mon the other side. They are available as follows:

NDC 51079-922-20 – Unit dose blister packages of 100 (10 cards of 10 tablets each).

The 200 mg tablets are green, round, functionally scored tablets debossed with C73above the score and blank below the score on one side of the tablet and Mon the other side. They are available as follows:

NDC 51079-749-20 – Unit dose blister packages of 100 (10 cards of 10 tablets each).

16.2 Storage and Handling

Store at 20° to 25°C (68° to 77°F). [See USP Controlled Room Temperature.]

Keep out of reach of children.

17 PATIENT COUNSELING INFORMATION

Discuss the following issues with patients and caregivers:

- Severe Neutropenia:
  - Instruct patients (and caregivers) beginning treatment with clozapine tablets about the risk of developing severe neutropenia and infection.
  - Instruct patients to immediately report to their physician any symptom or sign of infection (e.g., flu-like illness; fever; lethargy; general weakness or malaise; mucus membrane ulceration; skin, pharyngeal, vaginal, urinary, or pulmonary infection; or extreme weakness or lethargy) occurring at any time during clozapine tablets therapy, to aid in evaluation for neutropenia and to institute prompt and appropriate management [see Warnings and Precautions (5.1, 5.12, 5.14)] .
  - Inform patients and caregivers clozapine tablets are available only through a restricted program called the Clozapine REMS Program designed to ensure the required blood monitoring, in order to reduce the risk of developing severe neutropenia. Advise patients and caregivers of the importance of having blood tested as follows:
    - Weekly blood tests are required for the first 6 months.
    - An ANC is required every 2 weeks for the next 6 months if an acceptable ANC is maintained during the first 6 months of continuous therapy.
    - An ANC is required once every 4 weeks thereafter if an acceptable ANC is maintained during the second 6 months of continuous therapy.
  - Clozapine tablets are available only from certified pharmacies participating in the program. Provide patients (and caregivers) with website information and the telephone number on how to obtain the product (www.clozapineREMS.com or 1-888-586-0758) [see Warnings and Precautions (5.2)] .
- Orthostatic Hypotension, Bradycardia, and Syncope:Inform patients and caregivers about the risk of orthostatic hypotension and syncope, especially during the period of initial dose titration. Instruct them to strictly follow the clinician’s instructions for dosage and administration [see Dosage and Administration (2.2, 2.6)] . Advise patients to consult their clinician immediately if they feel faint, lose consciousness or have signs or symptoms suggestive of bradycardia or arrhythmia [see Warnings and Precautions (5.3)] .
- Seizures:Inform patients and caregivers about the significant risk of seizure during clozapine tablets treatment. Caution them about driving and any other potentially hazardous activity while taking clozapine tablets [see Warnings and Precautions (5.5)] .
- Gastrointestinal Hypomotility with Severe Complications:Educate patients and caregivers on the risks, prevention and treatment of clozapine-induced constipation, including medications to avoid when possible (e.g., drugs with anticholinergic activity). Encourage appropriate hydration, physical activity, and fiber intake and emphasize that prompt attention and treatment to the development of constipation or other gastrointestinal symptoms is critical in preventing severe complications. Advise patients and caregivers to contact their health care provider if they experience symptoms of constipation (e.g., difficulty passing stools, incomplete passage of stool, decreased bowel movement frequency) or other symptoms associated with gastrointestinal hypomotility (e.g., nausea, abdominal distension or pain, vomiting) [see Warnings and Precautions (5.8), Drug Interactions (7.1)] .
- QT Interval Prolongation:Advise patients to consult their clinician immediately if they feel faint, lose consciousness or have signs or symptoms suggestive of arrhythmia. Instruct patients to not take clozapine tablets with other drugs that cause QT interval prolongation. Instruct patients to inform their clinicians that they are taking clozapine tablets before any new drug [see Warnings and Precautions (5.10), Drug Interactions (7.1)] .
- Metabolic Changes (Hyperglycemia and Diabetes Mellitus, Dyslipidemia, Weight Gain):Educate patients and caregivers about the risk of metabolic changes and the need for specific monitoring. The risks include hyperglycemia and diabetes mellitus, dyslipidemia, weight gain, and cardiovascular reactions. Educate patients and caregivers about the symptoms of hyperglycemia (high blood sugar) and diabetes mellitus (e.g., polydipsia, polyuria, polyphagia, and weakness). Monitor all patients for these symptoms. Patients who are diagnosed with diabetes or have risk factors for diabetes (obesity, family history of diabetes) should have their fasting blood glucose monitored before beginning treatment and periodically during treatment. Patients who develop symptoms of hyperglycemia should have assessments of fasting glucose. Clinical monitoring of weight is recommended [see Warnings and Precautions (5.11)] .
- Interference with Cognitive and Motor Performance:Because clozapine tablets may have the potential to impair judgment, thinking, or motor skills, patients should be cautioned about operating hazardous machinery, including automobiles, until they are reasonably certain that clozapine tablets therapy does not affect them adversely [see Warnings and Precautions (5.17)] .
- Missed Doses and Re-Initiating Treatment:Inform patients and caregivers that if the patient misses taking clozapine tablets for more than 2 days, they should not restart their medication at the same dosage but should contact their physician for dosing instructions [see Dosage and Administration (2.5), Warnings and Precautions (5.1, 5.3)] .
- Pregnancy:Advise pregnant women to notify their healthcare provider if they become pregnant or intend to become pregnant during treatment with clozapine tablets. Advise patients that clozapine tablets may cause extrapyramidal and/or withdrawal symptoms (agitation, hypertonia, hypotonia, tremor, somnolence, respiratory distress, and feeding disorder) in a neonate. Advise patients that there is a pregnancy exposure registry that monitors pregnancy outcomes in women exposed to clozapine tablets during pregnancy [see Use in Specific Populations (8.1)].
- Lactation:Advise breastfeeding women using clozapine tablets to monitor infants for excess sedation and to seek medical care if they notice this sign. Inform breastfeeding women using clozapine tablets that their healthcare provider will monitor infants for neutropenia [see Use in Specific Populations (8.2)].
- Concomitant Medication:Advise patients to inform their healthcare provider if they are taking, or plan to take, any prescription or over-the-counter drugs; there is a potential for significant drug-drug interactions [see Dosage and Administration (2.6), Drug Interactions (7.1)] .

The brands listed are trademarks of their respective owners.

Manufactured for:
Mylan Pharmaceuticals Inc.
Morgantown, WV 26505 U.S.A.

Manufactured by:
Mylan Laboratories Limited
Hyderabad — 500 096, India

Distributed by:
Mylan Institutional Inc.
Rockford, IL 61103 U.S.A.

S-12767 R3
3/25

PRINCIPAL DISPLAY PANEL – 25 mg

NDC 51079-921-20

Clozapine
Tablets, USP
25 mg

Dispensing should be contingent upon ANC
results and should not exceed limits as
specified in the full product labeling.

100 Tablets (10 x 10)

Each tablet contains:
Clozapine, USP 25 mg

Usual Adult Dosage: See accompanying
prescribing information.

Store at 20° to 25°C (68° to 77°F). [See
USP Controlled Room Temperature.]

Code No.: MH/DRUGS/AD/089

Manufactured for:
Mylan Pharmaceuticals Inc.
Morgantown, WV 26505 U.S.A.

Made in India

Rx only

S-12722

Distributed by:

Mylan Institutional Inc.

Rockford, IL 61103 U.S.A.

This unit dose package is not child resistant.

For institutional use only.

Keep this and all drugs out of the reach of children.

This container provides light-resistance.

See window for lot number and expiration date.

PRINCIPAL DISPLAY PANEL – 100 mg

NDC 51079-922-20

Clozapine
Tablets, USP
100 mg

Dispensing should be contingent upon ANC
results and should not exceed limits as
specified in the full product labeling.

100 Tablets (10 x 10)

Each tablet contains:
Clozapine, USP 100 mg

Usual Adult Dosage: See accompanying
prescribing information.

Store at 20° to 25°C (68° to 77°F). [See
USP Controlled Room Temperature.]

Code No.: MH/DRUGS/AD/089

Manufactured for:
Mylan Pharmaceuticals Inc.
Morgantown, WV 26505 U.S.A.

Made in India

Rx only

S-12723

Distributed by:

Mylan Institutional Inc.

Rockford, IL 61103 U.S.A.

This unit dose package is not child resistant.

For institutional use only.

Keep this and all drugs out of the reach of children.

This container provides light-resistance.

See window for lot number and expiration date.

PRINCIPAL DISPLAY PANEL – 200 mg

NDC 51079-749-20

Clozapine
Tablets, USP
200 mg

Dispensing should be contingent upon ANC
results and should not exceed limits as
specified in the full product labeling.

100 Tablets (10 x 10)

Each tablet contains:
Clozapine, USP 200 mg

Usual Adult Dosage: See accompanying
prescribing information.

Store at 20° to 25°C (68° to 77°F). [See
USP Controlled Room Temperature.]

Code No.: MH/DRUGS/AD/089

Manufactured for:
Mylan Pharmaceuticals Inc.
Morgantown, WV 26505 U.S.A.

Made in India

Rx only

S-12724

Distributed by:

Mylan Institutional Inc.

Rockford, IL 61103 U.S.A.

This unit dose package is not child resistant.

For institutional use only.

Keep this and all drugs out of the reach of children.

This container provides light-resistance.

See window for lot number and expiration date.